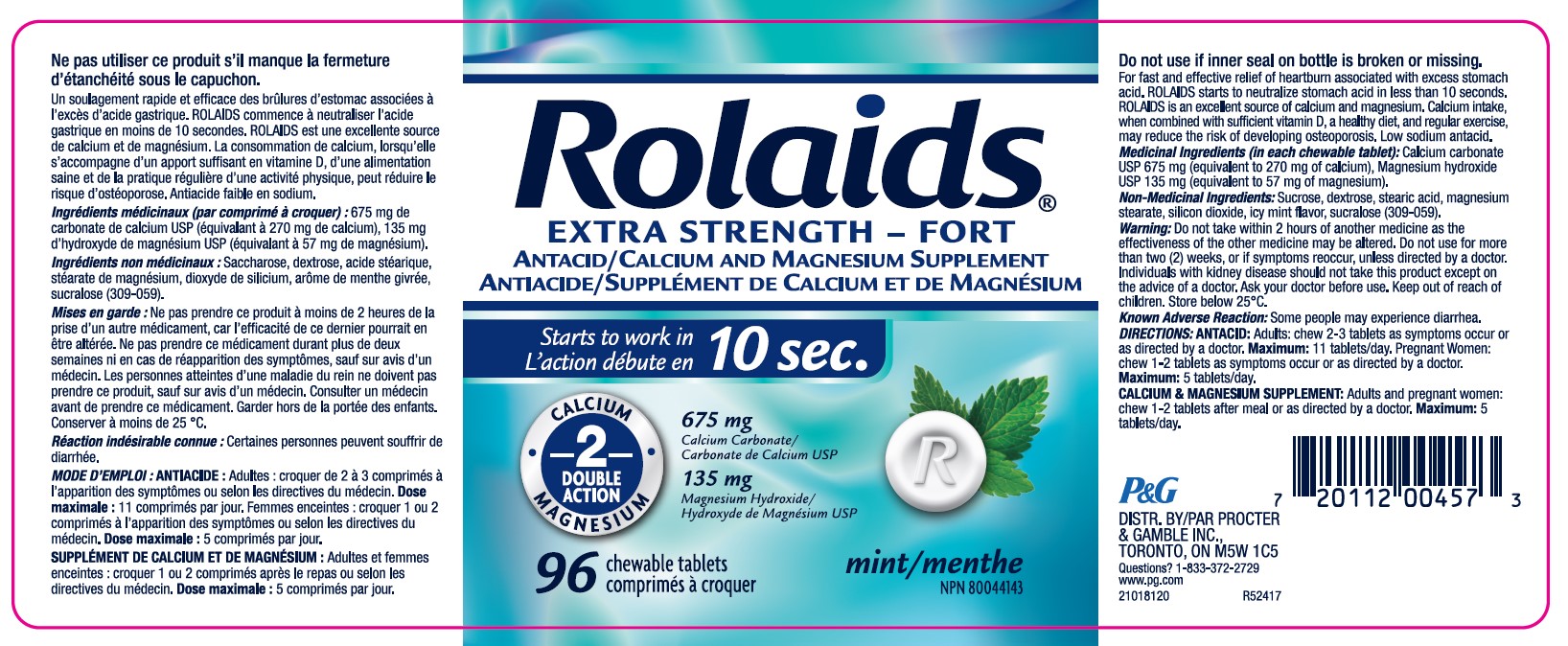 DRUG LABEL: Calcium Carbonate, Magnesium Hydroxide
NDC: 10267-0020 | Form: TABLET, CHEWABLE
Manufacturer: Contract Pharmacal Corp.
Category: otc | Type: HUMAN OTC DRUG LABEL
Date: 20250523

ACTIVE INGREDIENTS: CALCIUM CARBONATE 675 mg/1 1; MAGNESIUM HYDROXIDE 135 mg/1 1
INACTIVE INGREDIENTS: SUCRALOSE; STEARIC ACID; SILICON DIOXIDE; MALTODEXTRIN; MINT; DEXTROSE; MAGNESIUM STEARATE; SUCROSE

4446- Export